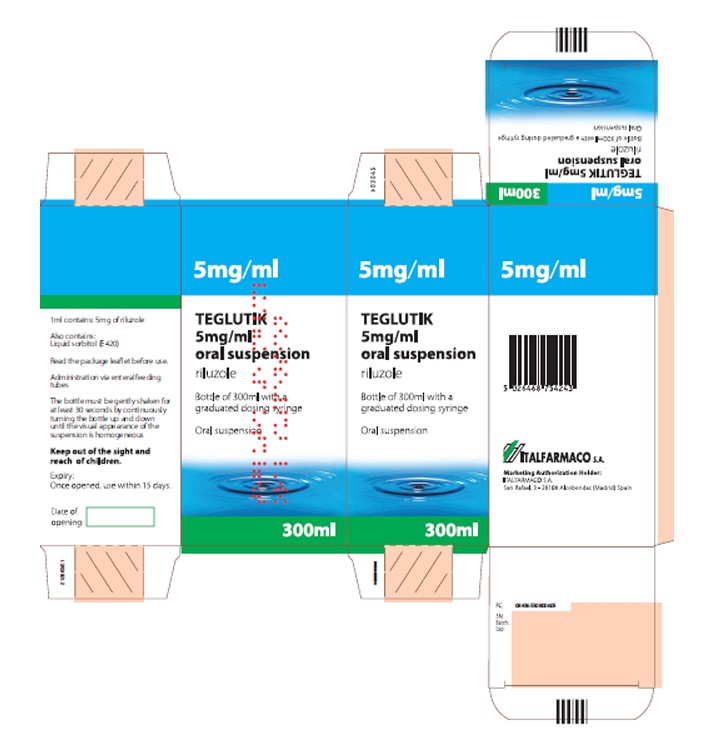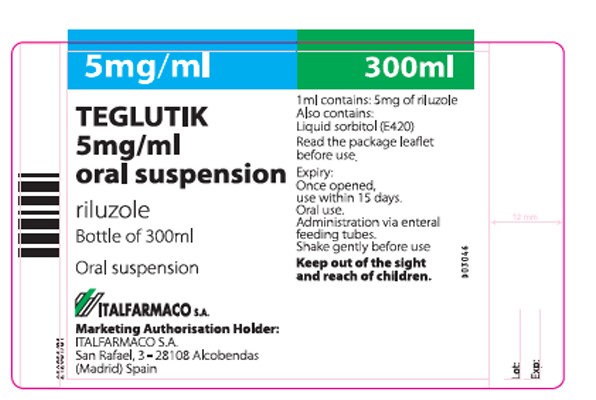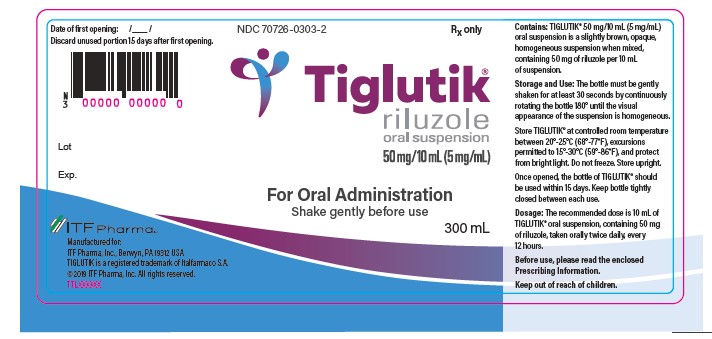 DRUG LABEL: Teglutik
NDC: 70726-0306 | Form: LIQUID
Manufacturer: EDW PHARMA
Category: prescription | Type: HUMAN PRESCRIPTION DRUG LABEL
Date: 20251231

ACTIVE INGREDIENTS: RILUZOLE 5 mg/1 mL
INACTIVE INGREDIENTS: MAGNESIUM ALUMINUM SILICATE; SORBITOL; POLYOXYL 20 CETOSTEARYL ETHER; WATER; SACCHARIN SODIUM; SILICON DIOXIDE; DIMETHICONE; SODIUM LAURYL SULFATE; XANTHAN GUM

Important Prescribing Information

May2024

Subject: Temporary importation of TEGLUTIK (riluzole oral suspension, 5 mg/mL) with English labeling to address drug shortage in the United States

Dear Health Care Provider,

The purpose of this letter is to inform you about a temporary importation in the United States (U.S.) of TEGLUTIK (riluzole 5 mg/mL oral suspension) with bottle and carton labels in English, in coordination with the U.S. Food and Drug Administration (FDA) to mitigate the current shortage of FDA-approved Tiglutik (riluzole oral suspension, 50 mg/10 mL) in the U.S. This temporary supply of TEGLUTIK is marketed and manufactured by Italfarmaco in Spain and is not FDA-approved.

Riluzole is indicated for the treatment of amyotrophic lateral sclerosis (ALS). Recently, Tiglutik was recalled in the U.S. market due to an out-of-specification test result for viscosity.

At this time, no other entity except EDW Pharma, Inc. (formerly Italfarmaco (ITF) Pharma, Inc.) is authorized by the FDA to import or distribute Italfarmaco's TEGLUTIK riluzole oral suspension in the U.S.

Effective immediately, and during this temporary period, EDW Pharma, Inc. will distribute the following presentation of riluzole oral suspension to address the critical shortage:

Product Name | Quantity | Descriptions | U.S. NDC number | Lot Number | Expiration Date
TEGLUTIK; riluzole oral | carton; suspension; (5 mg/mL) | 1 bottle per carton | Teglutik is presented; as a slightly brown,; opaque homogeneous oral; suspension after being; manually gently shaken.; TEGLUTIK is; available in a bottle; of 300 ml with a; plastic graduated oral dosing; syringe. The; syringe barrel is; graduated in; milliliters up to 10 ml. | 70726-0306-1 | 24008 | 04/2027

The safety profiles of the FDA-approved Tiglutik and imported TEGLUTIK products are comparable and no specific safety concerns emerged from the comparison of the two products.
Please refer to the side-by-side comparison of the labels (enclosed) for additional information.
Tiglutik is available only by prescription in the U.S. The imported lot does not have the statement "Rx only" on its labeling.

The barcode on the imported product label may not register accurately on the U.S. scanning systems. Institutions should manually input the imported product information into their systems and confirm that the barcode, if scanned, provides correct information. Alternative procedures should be followed to assure that the correct drug product is being used and administered to individual patients.

In addition, the package of the imported product does not include a product identifier as required under the Drug Supply Chain Security Act (DSCSA). Specifically, each package does not include the NDC, unique serial number, lot number, and expiration date in both human- readable and a two-dimensional data matrix barcode. Additionally, the imported product may not be accompanied with DSCSA-required product tracing documentation (transaction information, transaction history, and transaction statement).

Reporting Adverse Events

Health care providers and patients are encouraged to report adverse events and medication errors in patients taking TEGLUTIK to AnovoRx at 1-844-763-1198. You are encouraged to report negative side effects of prescription drugs to the FDA.

Adverse events or quality problems experienced with the use of this product may also be reported to the FDA's MedWatch Adverse Event Reporting Program either online, by regular mail, or by fax:

- Complete and submit the report Online: www.fda.gov/medwatch/report.htm
- Regular mail or Fax: Download form www.fda.gov/MedWatch/getforms.htm or call 1- 800-332-1088 to request a reporting form, then complete and return to the address on the pre-addressed form or submit by fax to 1-800-FDA-0178 (1-800-332-0178).

You may also contact AnovoRx at 1-844-763-1198 if you have any questions about the information contained in this letter or the safe and effective use of TEGLUTIK.

This letter is not intended as a complete description of the benefits and risks related to the use of TEGLUTIK. Please refer to the enclosed TEGLUTIK SmPC and Tiglutik USPI side-by- side comparison.

For additional information, please visit www.tiglutik.com and www.edwpharma.com.

Sincerely,

Peter Cook

CEO and President

EDW Pharma, Inc. (Formerly ITF Pharma, Inc.)

(UK Bottle TEXT) | (u.s. BOTTLE label - TEXT)
NAME OF THE MEDICINAL PRODUCT; TEGLUTIK 5 mg/ml oral suspension riluzole | NAME OF THE MEDICINAL PRODUCT; TIGLUTIK® riluzole oral suspension 50mg/10ml(5mg/ml)
STATEMENT OF ACTIVE SUBSTANCE(S); 1 ml contains: 5 mg of riluzole | STATEMENT OF ACTIVE SUBSTANCE(S); Contains: TIGLUTIK® 50 mg/10 mL (5 mg/mL)
LIST OF EXCIPIENTS; Also contains: liquid sorbitol (E420) | -------
PHARMACEUTICAL FORM AND CONTENTS; Oral suspension; Bottle of 300 ml | PHARMACEUTICAL FORM AND CONTENTS; s product is a ling Information.; TIGLUTIK® 50 mg/10 mL (5 mg/mL) oral suspension is a slightly brown, opaque,; homogeneous suspension when mixed, containing 50 mg of riluzole per 10 mL of suspension
METHOD AND ROUTE(S) OF ADMINISTRATION; Read the package leaflet before use; Oral use; Administration via enteral feeding tubes; Shake gently before use | METHOD AND ROUTE(S) OF ADMINISTRATION; Before use, please read the enclosed Prescribing Information.; For oral administration; Shake gently before use; The bottle must be gently shaken for at least 30 seconds by continuously rotating the bottle 180° until the visual appearance of the suspension is homogeneous.
DOSAGE; ----- | DOSAGE; The recommended dose is 10 mL of TIGLUTIK® oral suspension, containing 50 mg of riluzole, taken orally twice daily, every 12 hours.
SPECIAL WARNING THAT THE MEDICINAL PRODUCT MUST BE STORED OUT OF THE SIGHT AND REACH OF CHILDREN; Keep out of the sight and reach of children | SPECIAL WARNING THAT THE MEDICINAL PRODUCT MUST BE STORED OUT OF THE SIGHT AND REACH OF CHILDREN; Keep out of reach of children.
SPECIAL STORAGE CONDITIONS Expiry:; Once opened, use within 15 days | SPECIAL STORAGE CONDITIONS; Store TIGLUTIK® at controlled room temperature between 20°-25°C (68°-77°F), excursions permitted to 15°-30°C (59°-86°F) and protect from bright light.; Do not freeze. Store upright.; Once opened, the bottle of TIGLUTIK® should be used within 15 days. Keep bottle tightly closed between each use.
GENERAL CLASSIFICATION FOR SUPPLY; Medicinal product subject to medical prescription Hospital use | GENERAL CLASSIFICATION FOR SUPPLY; Rx only
NAME AND ADDRESS OF THE MARKETING AUTHORISATION HOLDER; Marketing Authorization Holder: ITALFARMACO S.A San Rafael, 3 28108 Alcobendas (Madrid) Spain | ITF Pharma Manufactured for:; ITF Pharma, Inc.; Berwyn, PA 19312 USA; TIGLUTIK is a registered trademark of Italfarmaco S.A.; ©2019 ITF Pharma, Inc. All rights reserved.; TOCXXXXXX